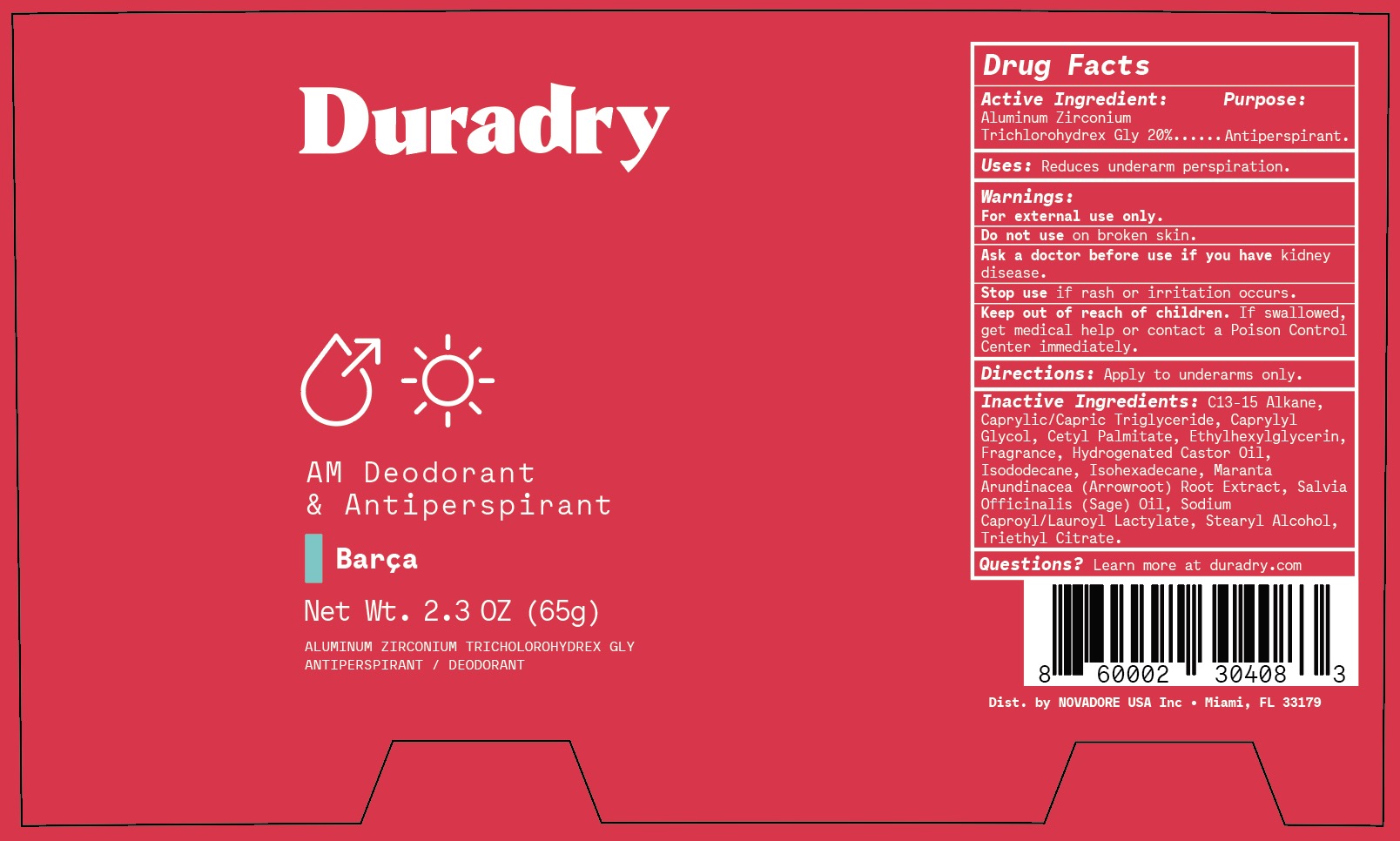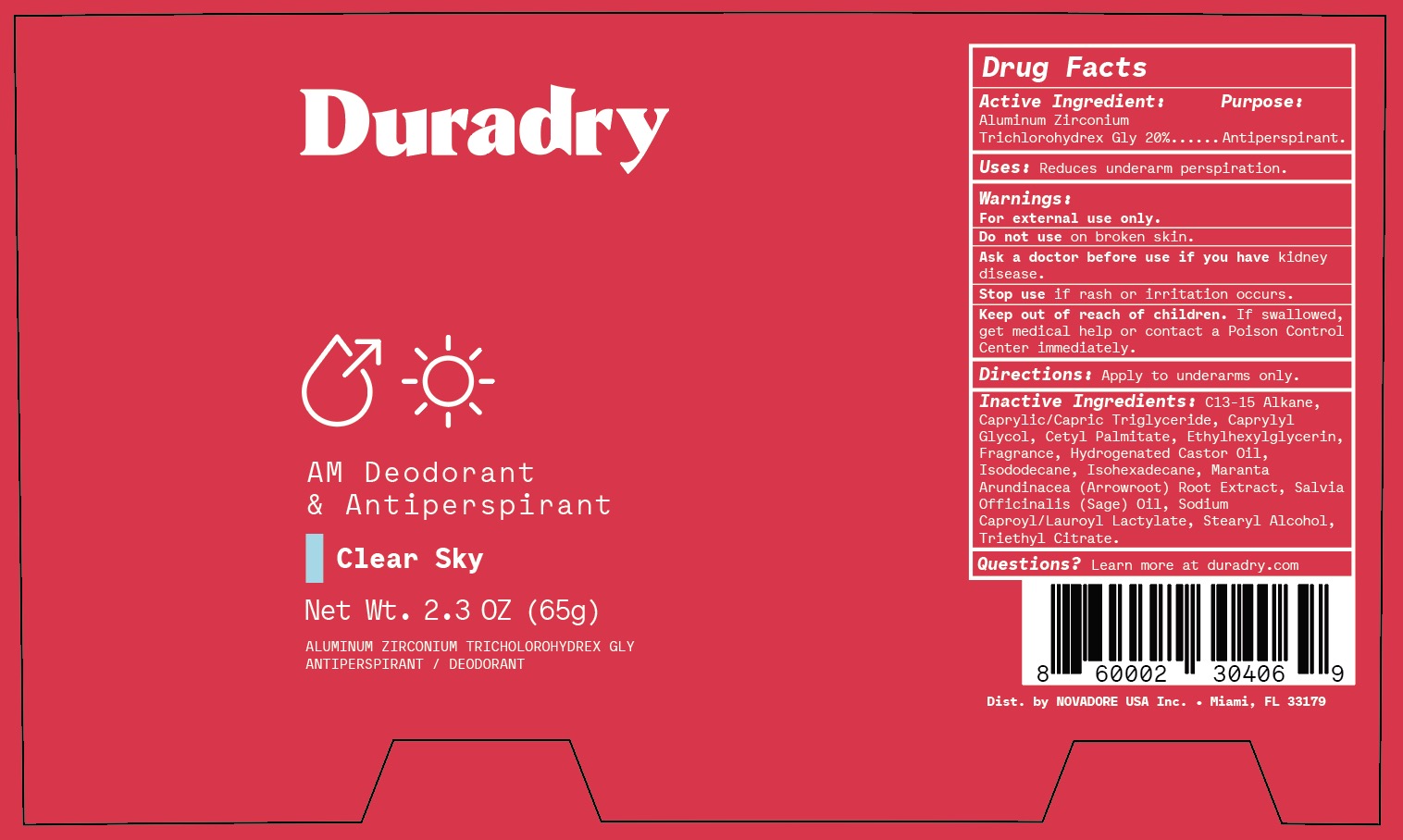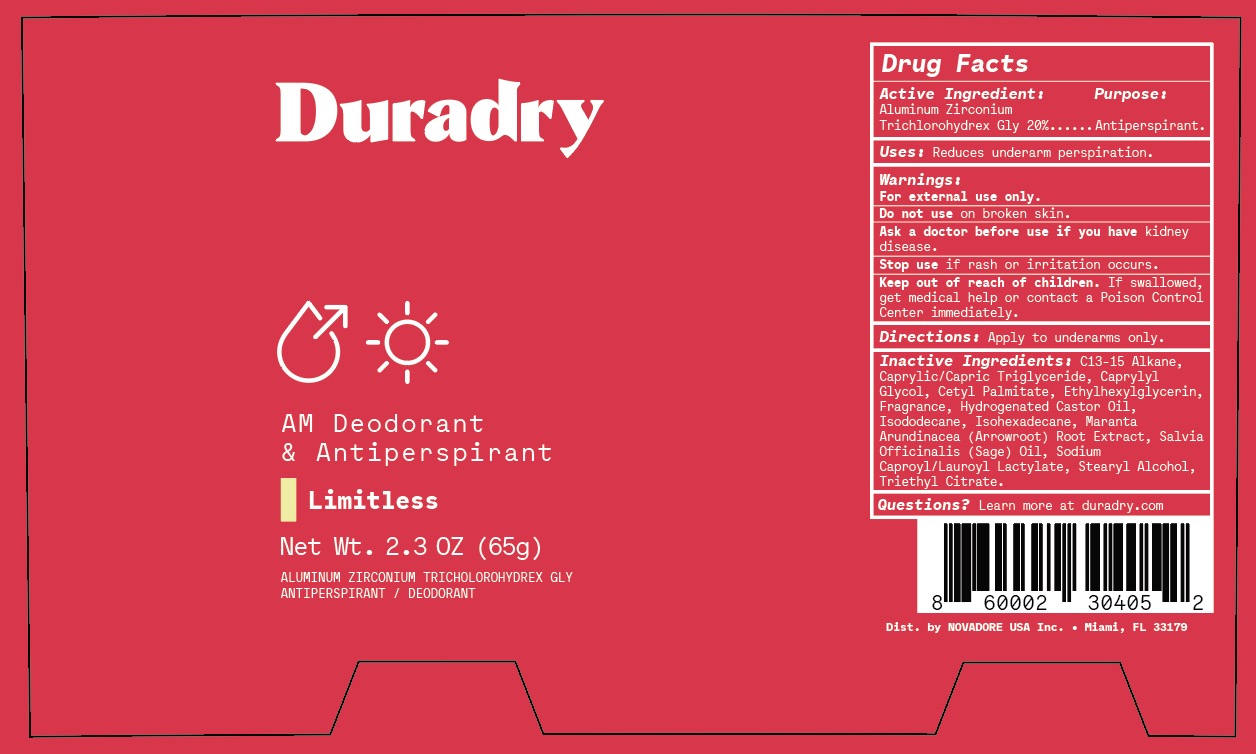 DRUG LABEL: Duradry Antiperspirant Deodorant Stick
NDC: 69990-316 | Form: STICK
Manufacturer: NOVADORE USA Inc
Category: otc | Type: HUMAN OTC DRUG LABEL
Date: 20251111

ACTIVE INGREDIENTS: ALUMINUM ZIRCONIUM TRICHLOROHYDREX GLY 20 g/100 g
INACTIVE INGREDIENTS: STEARYL ALCOHOL; MARANTA ARUNDINACEA ROOT; HYDROGENATED CASTOR OIL; TRIETHYL CITRATE; ISODODECANE; C13-15 ALKANE; FRAGRANCE 13576; ISOHEXADECANE; CAPRYLIC/CAPRIC/LAURIC TRIGLYCERIDE; ETHYLHEXYLGLYCERIN; SALVIA OFFICINALIS ROOT; SODIUM CAPROYL LACTYLATE; CETYL PALMITATE; CAPRYLYL GLYCOL

Duradry Antiperspirant Deodorant Stick

Active Ingredient

Aluminum Zirconium Trichlorohydrex Glycine 20%

Purpose

Antiperspirant

Uses

Reduces underarm perspiration

Warnings

For external use only.

Stop use if rash or irritation occurs.

Do not use

On broken skin

Ask a doctor before use

if you have kidney disease

Keep out of reach of children

If swallowed, get medical help or contact a Poison Control Center immediately.

Directions

Apply to underarms only

Inactive Ingredients

C13-15 Alkane, Caprylic/Capric Triglyceride, Caprylyl Glycol, Cetyl Palmitate, Ethylhexylglycerin, Fragrance, Hydrogenated Castor Oil, Isododecane, Isohexadecane, Maranta Arundinacea (Arrowroot) Root Extract, Salvia Officinalis (Sage) Oil, Sodium Caproyl/Lauroyl Lactylate, Stearyl Alcohol, Triethyl Citrate.

Questions?

Learn more at duradry.com